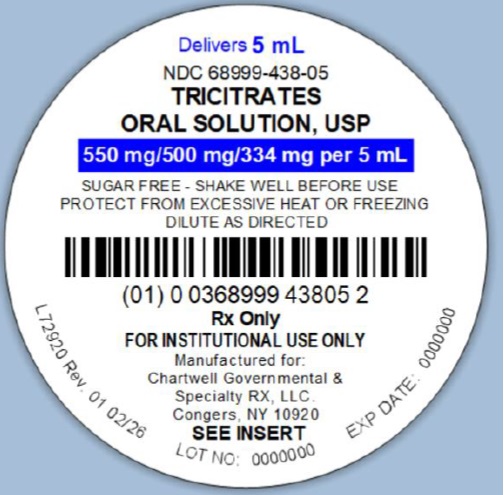 DRUG LABEL: Tricitrates
NDC: 68999-438 | Form: SOLUTION
Manufacturer: Chartwell Governmental & Specialty RX, LLC.
Category: prescription | Type: HUMAN PRESCRIPTION DRUG LABEL
Date: 20260225

ACTIVE INGREDIENTS: POTASSIUM CITRATE 550 mg/5 mL; SODIUM CITRATE 500 mg/5 mL; CITRIC ACID MONOHYDRATE 334 mg/5 mL
INACTIVE INGREDIENTS: SACCHARIN SODIUM; SODIUM BENZOATE; SORBITOL SOLUTION; FD&C YELLOW NO. 6; WATER

Tricitrates Oral Solution, USP
Rx ONLY

DESCRIPTION

Tricitrates Oral Solution, USP is a stable orange colored and cherry flavored oral systemic alkalizer containing potassium citrate, sodium citrate, and citric acid in a sugar-free, non-alcoholic base.

Tricitrates Oral Solution, USP contains in each teaspoonful (5 mL):

Potassium Citrate Monohydrate, USP 550 mg

Sodium Citrate Dihydrate, USP 500 mg

Citric Acid Monohydrate, USP 334 mg

Each mL contains 1 mEq potassium ion and 1 mEq sodium ion and is equivalent to 2 mEq bicarbonate (HCO3).

Inactive Ingredients: saccharin sodium, sodium benzoate, sorbitol solution, FD&C yellow # 6, wild cherry flavor, and purified water.

ACTIONS

Potassium citrate and sodium citrate are absorbed and metabolized to potassium bicarbonate and sodium bicarbonate, thus acting as systemic alkalizers. The effects are essentially those of chlorides before absorption and those of bicarbonates subsequently. Oxidation is virtually complete so that less than 5% of the citrates are excreted in the urine unchanged.

INDICATIONS AND ADVANTAGES

Tricitrates oral solution is an effective alkalinizing agent useful in those conditions where long-term maintenance of an alkaline urine is desirable, such as in patients with uric acid and cystine calculi of the urinary tract. In addition, it is a valuable adjuvant when administered with uricosuric agents in gout therapy, since urates tend to crystallize out of an acid urine. It is also effective in correcting the acidosis of certain renal tubular disorders. This product is highly concentrated, and when administered after meals and before bedtime, allows one to maintain an alkaline urine pH around the clock, usually without the necessity of a 2 A.M. dose. This product alkalinizes the urine without producing a systemic alkalosis in recommended dosage. It is highly palatable, pleasant tasting, and tolerable, even when administered for long periods. Potassium citrate and sodium citrate do not neutralize the gastric juice or disturb digestion.

CONTRAINDICATIONS

Severe renal impairment with oliguria or azotemia, untreated Addison's disease, or severe myocardial damage. In certain situations, when patients are on a sodium-restricted diet, the use of potassium citrate may be preferable; or, when patients are on a potassium-restricted diet, the use of sodium citrate may be preferable.

PRECAUTIONS AND WARNINGS

Should be used with caution by patients with low urinary output or reduced glomerular filtration rates unless under the supervision of a physician. Aluminum-based antacids should be avoided in these patients. Patients should be directed to dilute adequately with water and, preferably, to take each dose after meals, to minimize the possibility of gastrointestinal injury associated with oral ingestion of potassium salt preparations and to avoid saline laxative effect. Sodium salts should be used cautiously in patients with cardiac failure, hypertension, peripheral and pulmonary edema, and toxemia of pregnancy.

Concurrent administration of potassium-containing medication, potassium-sparing diuretics, angiotensin-converting enzyme (ACE) inhibitors, or cardiac glycosides may lead to toxicity. Periodic examination and determinations of serum electrolytes, particularly serum bicarbonate level, should be carried out in those patients with renal disease in order to avoid these complications.

ADVERSE REACTIONS

Tricitrates oral solution is generally well tolerated without any unpleasant side effects when given in recommended doses to patients with normal renal function and urinary output. However, as with any alkalinizing agent, caution must be used in certain patients with abnormal renal mechanisms to avoid development of hyperkalemia or alkalosis, especially in the presence of hypocalcemia. Potassium intoxication causes listlessness, weakness, mental confusion, and tingling of extremities.

DOSAGE AND ADMINISTRATION

Tricitrates oral solution should be taken diluted in water, followed by additional water, if desired. Palatability is enhanced if chilled before taking.

Usual Adult Dose

3 to 6 teaspoonfuls (15 to 30 mL), diluted in water, four times a day, after meals and at bedtime, or as directed by a physician.

Usual Pediatric Dose

1 to 3 teaspoonfuls (5 to 15 mL), diluted in water, four times a day, after meals and at bedtime, or as directed by a physician.

Usual Dosage Range

2 to 3 teaspoonfuls (10 to 15 mL), diluted with water, taken four times a day, will usually maintain a urinary pH of 6.5-7.4. 3 to 4 teaspoonfuls (15 to 20 mL), diluted with water, taken four times a day, will usually maintain a urinary pH of 7.0-7.6 throughout most of the 24 hours without unpleasant side effects. To check urine pH, HYDRION Paper (pH 6.0-8.0) or NITRAZINE Paper (pH 4.5-7.5) are available and easy to use.

OVERDOSAGE

Overdosage with sodium salts may cause diarrhea, nausea and vomiting, hypernoia, and convulsions. Overdosage with potassium salts may cause hyperkalemia and alkalosis, especially in the presence of renal disease.

HOW SUPPLIED

Tricitrates Oral Solution, USP (orange colored, cherry flavored) is supplied in the following oral dosage form:

5 mL Unit-Dose Cup NDC 68999-438-05

20 Unit-Dose Cups of 5 mL NDC 68999-438-24

STORAGE

Store at controlled room temperature, 20° to 25°C (68° to 77°F). Protect from excessive heat and freezing.

SHAKE WELL BEFORE USING.

Manufactured for:

Chartwell Governmental & Specialty RX, LLC.

Congers, NY 10920

L72922

Rev. 02/2026

PACKAGE LABEL-PRINCIPAL DISPLAY PANEL

Tricitrates Oral Solution, USP - NDC 68999-438-05 - 5 mL Unit-Dose Cup Label